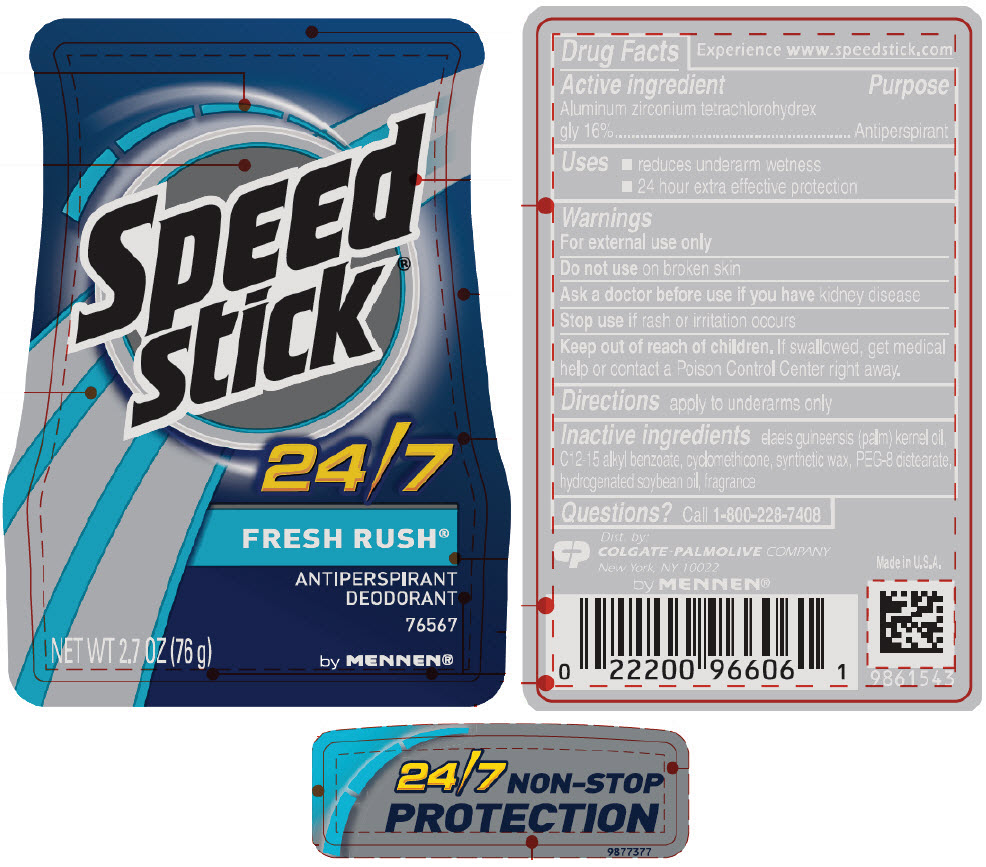 DRUG LABEL: Speed Stick
NDC: 35000-662 | Form: STICK
Manufacturer: COLGATE PALMOLIVE COMPANY
Category: otc | Type: HUMAN OTC DRUG LABEL
Date: 20191216

ACTIVE INGREDIENTS: ALUMINUM ZIRCONIUM TETRACHLOROHYDREX GLY 160 mg/1 g
INACTIVE INGREDIENTS: PALM KERNEL OIL; ALKYL (C12-15) BENZOATE; CYCLOMETHICONE; PEG-8 DISTEARATE; HYDROGENATED SOYBEAN OIL

Speed
stick®
24/7
FRESH RUSH®

Drug Facts

Active ingredient

Aluminum zirconium tetrachlorohydrex gly 16%

Purpose

Antiperspirant

Use

reduces underarm wetness

Warnings

For external use only

Do not use on broken skin

Ask a doctor before use if you have kidney disease

Stop use if rash or irritation occurs

Keep out of reach of children. If swallowed, get medical help or contact a Poison Control Center right away.

Directions

apply to underarms only

Inactive ingredients

elaeis guineensis (palm) kernel oil, C12-15 alkyl benzoate, cyclomethicone, synthetic wax, PEG-8 distearate, hydrogenated soybean oil, fragrance

Questions?

Call toll-free 1-800-228-7408

Dist. by:
COLGATE-PALMOLIVE COMPANY
New York, NY 10022

www.speedstick.com

PRINCIPAL DISPLAY PANEL - 76 g Container Label

Speed
stick®

24/7

FRESH RUSH®

ANTIPERSPIRANT
DEODORANT

76567

NET WT 2.7 OZ (76 g)

by MENNEN®